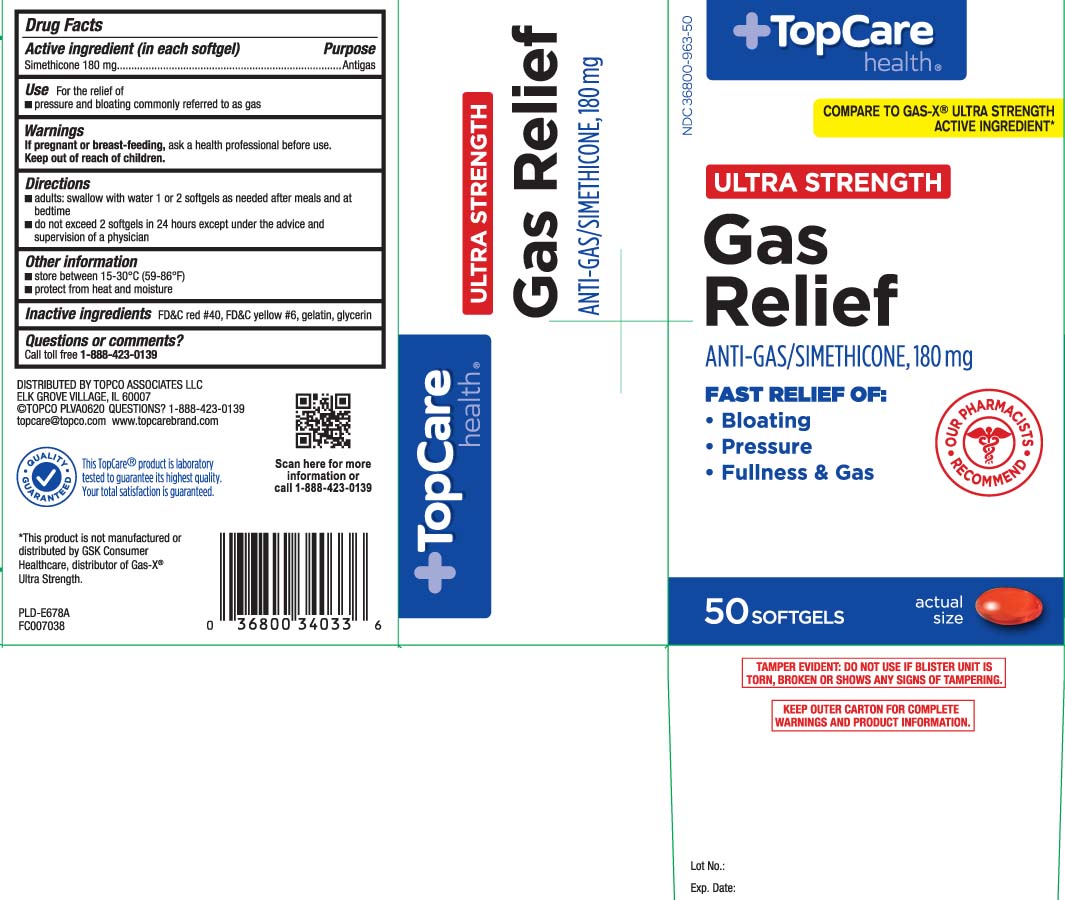 DRUG LABEL: Gas Relief
NDC: 36800-963 | Form: CAPSULE, LIQUID FILLED
Manufacturer: TOP CARE (Topco Associates LLC)
Category: otc | Type: HUMAN OTC DRUG LABEL
Date: 20241113

ACTIVE INGREDIENTS: DIMETHICONE 180 mg/1 1
INACTIVE INGREDIENTS: FD&C YELLOW NO. 6; GELATIN; GLYCERIN; FD&C RED NO. 40

Drug Facts

Active ingredient (in each softgel)

Simethicone 180 mg

Purpose

Antigas

Use

For the relief of

- pressure and bloating commonly referred to as gas

Warnings

If pregnant or breast-feeding,

ask a health care professional before use.

Directions

- adult: swallow with water 1 or 2 softgels as needed after meals and at bedtime
- do not exceed 2 softgels in 24 hours except under the advice and supervision of a physician

Other information

- store between 15-30ºC (59-86ºF)
- protect from heat and moisture

Inactive ingredients

FD&C red #40*,FD&C yellow # 6, gelatin, glycerin

Questions or comments?

Calltoll free 1-888-423-0139

Principal Display Panel

COMPARE TO GAS-X® ULTRA STRENGTH ACTIVE NGREDIENT*

ULTRA STRENGTH

Gas Relief

ANTI-GAS/SIMETHICONE, 180 mg

FAST RELIEF OF

- Bloating
- Pressure
- Fullness & Gas

SOFTGELS

**This product is not manufactured or distributed by GSK Consumer Healthcare, distributor of Gas-X® Ultra Strength.

TAMPER EVIDENT: DO NOT USE IF BLISTER UNIT IS TORN, BROKEN OR SHOWS ANY SIGNS OF TAMPERING.

KEEP OUTER CARTON FOR COMPLETE WARNINGS AND PRODUCT INFORMATION.

DISTRIBUTED BY TOPCO ASSOCIATES LLC

ELK GROVE VILLAGE, IL 60007

www.topcarebrand.com

Package Label

TOPCARE HEALTH Ultra Strength Gas Relief